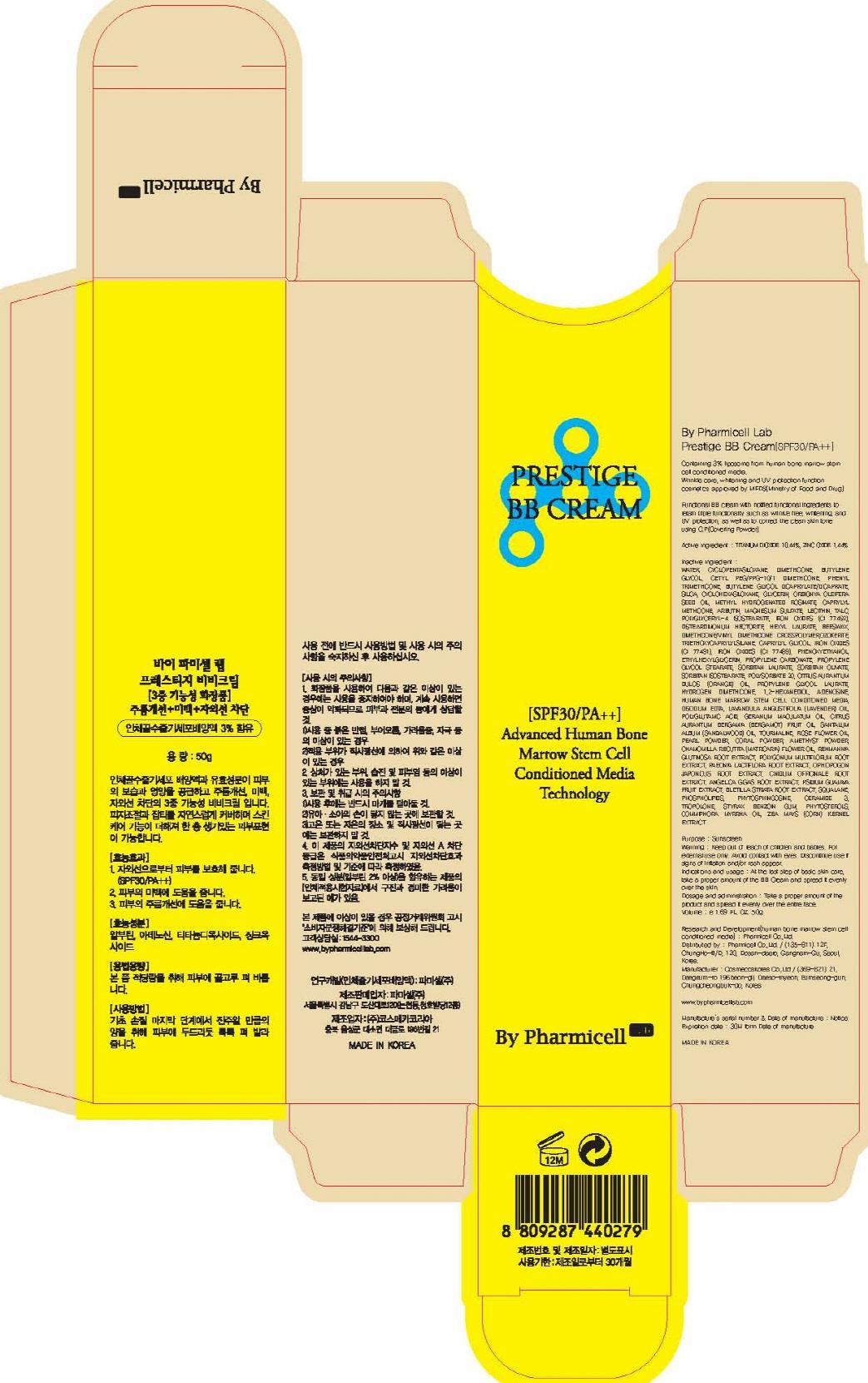 DRUG LABEL: By Pharmicell Lab Prestige BB
NDC: 60949-040 | Form: CREAM
Manufacturer: Pharmicell Co., Ltd.
Category: otc | Type: HUMAN OTC DRUG LABEL
Date: 20130707

ACTIVE INGREDIENTS: TITANIUM DIOXIDE 5.22 g/50 g; ZINC OXIDE 0.72 g/50 g
INACTIVE INGREDIENTS: WATER; DIMETHICONE

ACTIVE INGREDIENT

Active ingredient : TITANIUM DIOXIDE 10.44%, ZINC OXIDE 1.44%

INACTIVE INGREDIENT

Inactive ingredient : WATER, CYCLOPENTASILOXANE, DIMETHICONE, BUTYLENE GLYCOL, CETYL PEG/PPG-10/1 DIMETHICONE, PHENYL TRIMETHICONE, BUTYLENE GLYCOL DICAPRYLATE/DICAPRATE, SILICA, CYCLOHEXASILOXANE, GLYCERIN, ORBIGNYA OLEIFERA SEED OIL, METHYL HYDROGENATED ROSINATE, CAPRYLYL METHICONE, ARBUTIN, MAGNESIUM SULFATE, LECITHIN, TALC, POLYGLYCERYL-4 ISOSTEARATE, IRON OXIDES (CI 77492), DISTEARDIMONIUM HECTORITE, HEXYL LAURATE, BEESWAX, DIMETHICONE/VINYL DIMETHICONE CROSSPOLYMER, OZOKERITE, TRIETHOXYCAPRYLYLSILANE, CAPRYLYL GLYCOL, IRON OXIDES (CI 77491), IRON OXIDES (CI 77499), PHENOXYETHANOL, ETHYLHEXYLGLYCERIN, PROPYLENE CARBONATE, PROPYLENE GLYCOL STEARATE, SORBITAN LAURATE, SORBITAN OLIVATE, SORBITAN ISOSTEARATE, POLYSORBATE 20, CITRUS AURANTIUM DULCIS (ORANGE) OIL, PROPYLENE GLYCOL LAURATE, HYDROGEN DIMETHICONE, 1,2-HEXANEDIOL, ADENOSINE, HUMAN BONE MARROW STEM CELL CONDITIONED MEDIA, DISODIUM EDTA, LAVANDULA ANGUSTIFOLIA (LAVENDER) OIL, POLYGLUTAMIC ACID, GERANIUM MACULATUM OIL, CITRUS AURANTIUM BERGAMIA (BERGAMOT) FRUIT OIL, SANTALUM ALBUM (SANDALWOOD) OIL, TOURMALINE, ROSE FLOWER OIL, PEARL POWDER, CORAL POWDER, AMETHYST POWDER, CHAMOMILLA RECUTITA (MATRICARIA) FLOWER OIL, REHMANNIA GLUTINOSA ROOT EXTRACT, POLYGONUM MULTIFLORUM ROOT EXTRACT, PAEONIA LACTIFLORA ROOT EXTRACT, OPHIOPOGON JAPONICUS ROOT EXTRACT, CNIDIUM OFFICINALE ROOT EXTRACT, ANGELICA GIGAS ROOT EXTRACT, PSIDIUM GUAJAVA FRUIT EXTRACT, BLETILLA STRIATA ROOT EXTRACT, SQUALANE, PHOSPHOLIPIDS, PHYTOSPHINGOSINE, CERAMIDE 3, TROPOLONE, STYRAX BENZOIN GUM, PHYTOSTEROLS, COMMIPHORA MYRRHA OIL, ZEA MAYS (CORN) KERNEL EXTRACT

PURPOSE

Purpose : Sunscreen

WARNINGS

Warning : Keep out of reach of children and babies. For external use only. Avoid contact with eyes. Discontinue use if signs of irritation and/or rash appear.

Keep out of reach of children and babies.

Indications and usage : At the last step of basic skin care, take a proper amount of the BB Cream and spread it evenly over the skin.

Dosage and administration : Take a proper amount of the product and spread it evenly over the entire face.